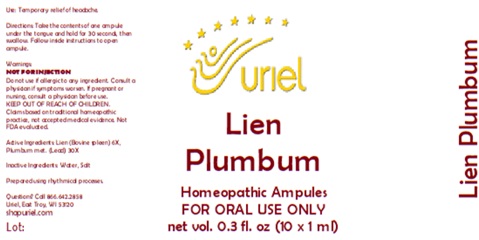 DRUG LABEL: Lien Plumbum
NDC: 48951-6035 | Form: LIQUID
Manufacturer: Uriel Pharmacy Inc.
Category: homeopathic | Type: HUMAN OTC DRUG LABEL
Date: 20260227

ACTIVE INGREDIENTS: BOS TAURUS SPLEEN 6 [hp_X]/1 mL; LEAD 30 [hp_X]/1 mL
INACTIVE INGREDIENTS: WATER; SODIUM CHLORIDE

Lien Plumbum

PURPOSE

Use: Temporary relief of headache.

INDICATIONS AND USAGE

FOR ORAL USE ONLY

DOSAGE AND ADMINISTRATION

Directions: Take the contents of one ampule under the tongue and hold for 30 seconds, then swallow. Follow inside instructions to open ampule.

Warnings:
NOT FOR INJECTION
Do not use if allergic to any ingredient. Consult a physician if symptoms worsen. If pregnant or nursing, consult a physician before use.
Claims based on traditional homeopathic practice, not accepted medical evidence. Not FDA evaluated.

KEEP OUT OF REACH OF CHILDREN.

ACTIVE INGREDIENT

Active Ingredients: Lien (Bovine spleen) 6X, Plumbum met. (Lead) 30X

Inactive Ingredients: Water, Salt

Prepared using rhythmical processes.

Questions? Call 866.642.2858
Uriel, East Troy, WI 53120
shopuriel.com